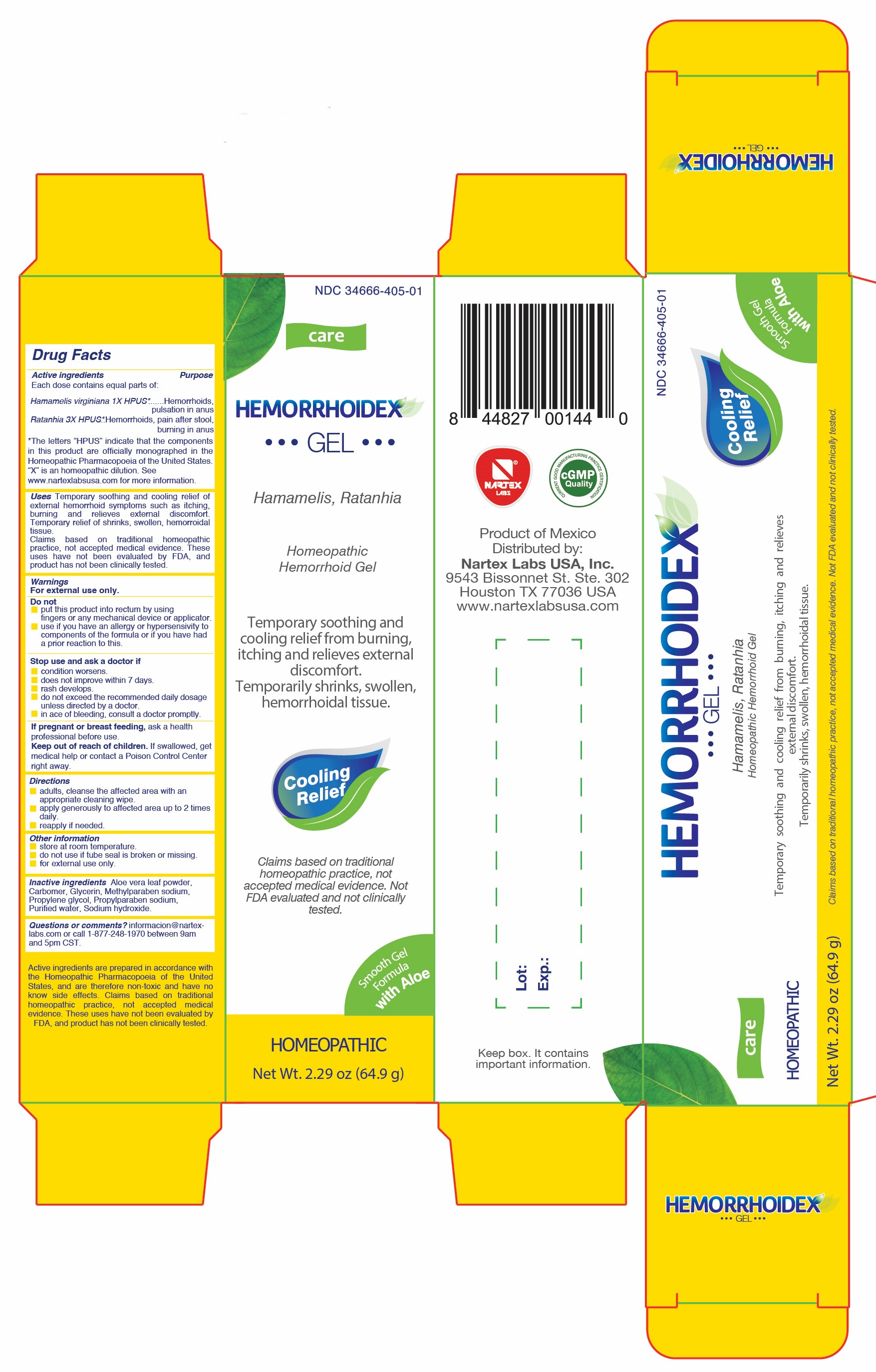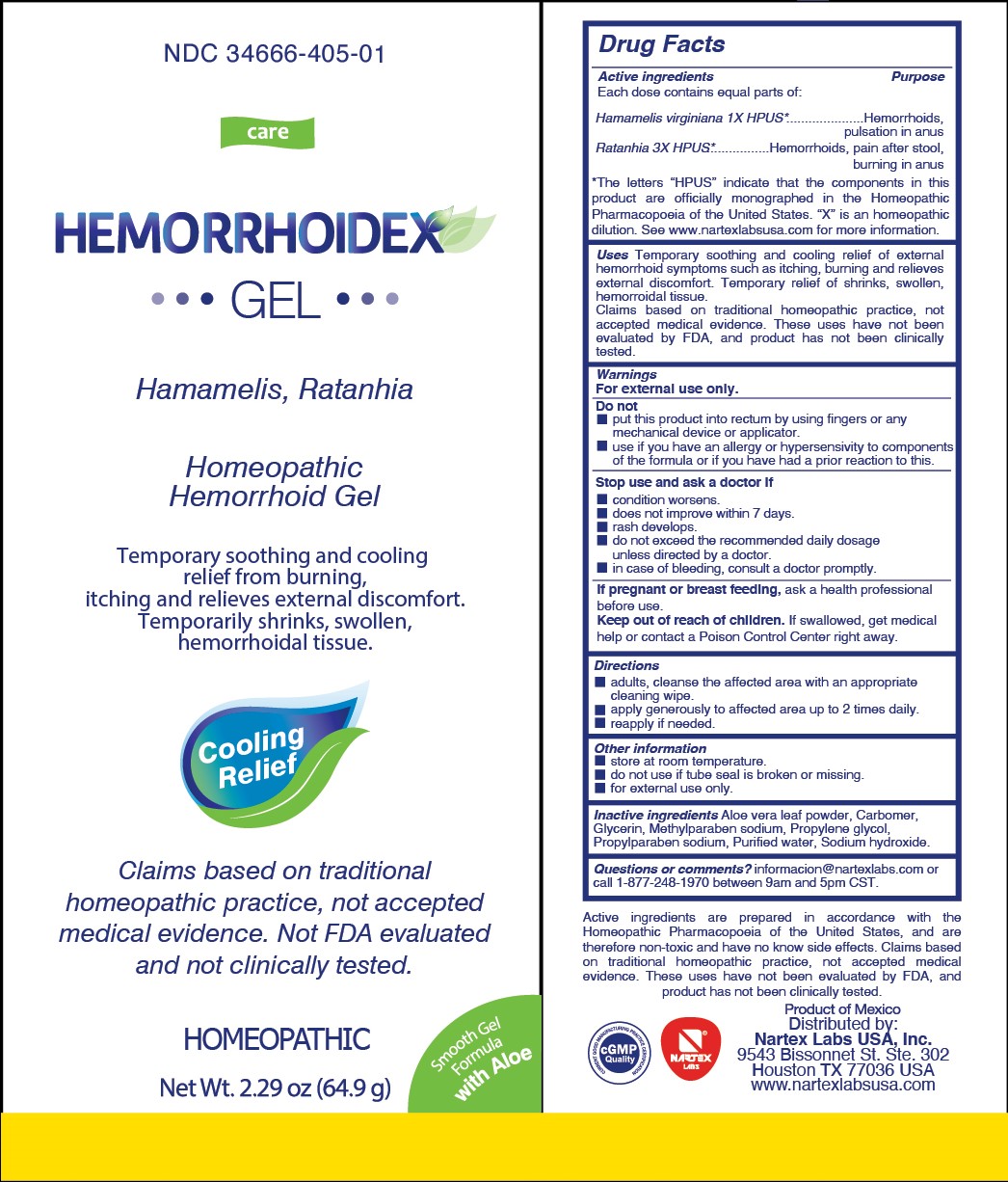 DRUG LABEL: Hemorrhoidex
NDC: 34666-405 | Form: GEL
Manufacturer: Nartex Laboratorios Homeopaticos, S.A. de C.V.
Category: homeopathic | Type: HUMAN OTC DRUG LABEL
Date: 20250418

ACTIVE INGREDIENTS: HAMAMELIS VIRGINIANA ROOT BARK/STEM BARK 1 [hp_X]/64.9 g; KRAMERIA LAPPACEA ROOT 3 [hp_X]/64.9 g
INACTIVE INGREDIENTS: ALOE VERA LEAF; CARBOMER HOMOPOLYMER, UNSPECIFIED TYPE; GLYCERIN; PROPYLPARABEN SODIUM; METHYLPARABEN SODIUM; WATER; PROPYLENE GLYCOL; SODIUM HYDROXIDE

Hemorrhoidex Gel

Active ingredients

Each dose contains equal parts of:

Hamamelis virginiana 1X HPUS*

Ratanhia 3X HPUS*

*The letters "HPUS" indciate that the components in the product are officially monographed in the Homeopathic Pharmacopoeia of the United States. "X" is an homeopathic dilution. See www.nartexlabsusa.com for more information.

Purpose

Each dose contains equal parts of:

Hamamelis virginiana 1X HPUS*............Hemorrhoids, pulsation in anus

Ratanhia 3X HPUS*....................Hemorrhoids, pain after stool, burning in anus

*The letters "HPUS" indciate that the components in the product are officially monographed in the Homeopathic Pharmacopoeia of the United States. "X" is an homeopathic dilution. See www.nartexlabsusa.com for more information.

Uses

Temporary soothing and cooling relief of external hemorrhoid symptoms such as itching, burning and relieves external discomfort. Temporary relief of shrinks, swollen, hemorrhoidal tissue.

Claims based on traditional homeopathic practice, not accepted medical evidence. These uses have not been evaluated by FDA, and product has not been clincially tested.

Warnings

For external use only.

Do not

- put this product into rectum by using fingers or any mechanical device or applicator.
- use if you have an allergy or hypersenstivity to components of the formula or if you have had a prior reaction to this.

Stop use and aska doctor if

- condition worsens.
- does not improve within 7 days.
- rash develops.
- do not exceed the recommended daily dosage unless directed by a doctor.
- in case of bleeding, consult a doctor promptly.

PREGNANCY OR BREAST FEEDING

If pregnant or breast feeding,ask a health professional before use.

Keep out of reach of children.If swallowed, get medical help or contact a Poison Control Center right away.

Directions

- adults, cleanse the affected area with an appropriate cleaning wipe.
- apply generously to affected area up to 2 times daily.
- reapply if needed.

Other information

- store at room temperature
- do not use if tube seal is broken or missing
- for external use only

Inactive ingredients

Aloe vera leaf powder, Carbomer, Glycerin, Methylparaben sodium, Propylene glycol, Propylparaben sodium, Purified water, Sodium hydroxide.

Questions or comments?

informacion@nartex-labs.com or call 1-877-248-1970 between 9am and 5pm CST.

PACKAGE LABEL

NDC 34666-405-01

care

Hemorrhoidex Gel

Hamamelis, Ratanhia

Homeopathic Hemorrhoid Gel

Temporary soothing and cooling relief from burning, itching and relieves external discomfort. Temporarily shrinks, swollen, hemorrhoidal tissue.

Cooling Relief

Claims based on traditional homeopathic practice, not accepted medical evidence. Not FDA evaluated and not clinically tested.

Smooth Gel Formula with Aloe

Homeopathic

Net Wt. 2.29 oz (64.9 g)